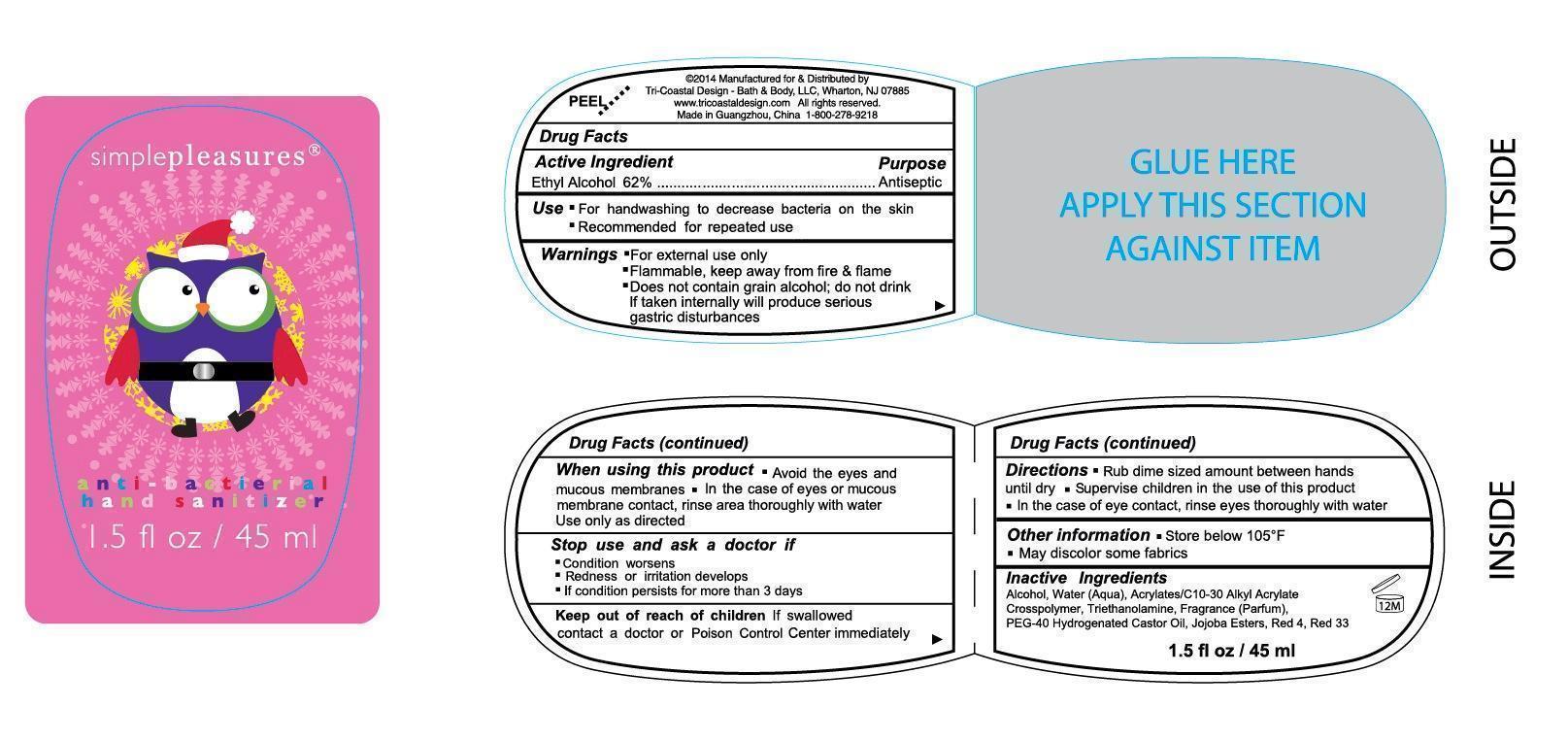 DRUG LABEL: anti-bacterial Hand Cleanser
NDC: 49852-301 | Form: LIQUID
Manufacturer: Tri-Coastal Design Company Inc.
Category: otc | Type: HUMAN OTC DRUG LABEL
Date: 20180101

ACTIVE INGREDIENTS: ALCOHOL 62 g/100 mL
INACTIVE INGREDIENTS: WATER; CARBOMER INTERPOLYMER TYPE A (55000 CPS); TROLAMINE; POLYOXYL 40 HYDROGENATED CASTOR OIL; HYDROLYZED JOJOBA ESTERS (ACID FORM); FD&C RED NO. 4; D&C RED NO. 33

Drug Facts

Active Ingredient

Ethyl Alcohol 62%

Purpose

Antiseptic

Uses

- For handwashing to decrease bacteria on the skin
- Recommended for repeated use

Warnings

- For external use only
- Flammable, keep away from fire and flame
- Does not contain grain alcohol; do not drink, if taken internally will produce serious gastric disturbances

When using this product

- Avoid the eyes and mucous membranes
- In the case of eyes or mucous membrane contact; rinse area thoroughly with water Use only as directed

Stop use and ask a doctor if

- Condition worsens
- Redness or irritation develops
- If condition persists for more than 3 days

Keep out of reach of children

If swallowed contact a doctor or Poison Control Center immediately.

Directions

- Rub dime sized amount between hands until dry
- Supervise children in the use of this product
- in the case of eye contact, rinse eyes thoroughly with water

Other information

- Store below 105F
- May discolor some fabrics

Inactive Ingredients

Water (Aqua), Acrylates/C10-30 Alkyl Acrylate Crosspolymer, Triethanolamine, Fragrance (Parfum), PEG-40 Hydrogenated Castor Oil, Jojoba Esters, Red 4, Red 33